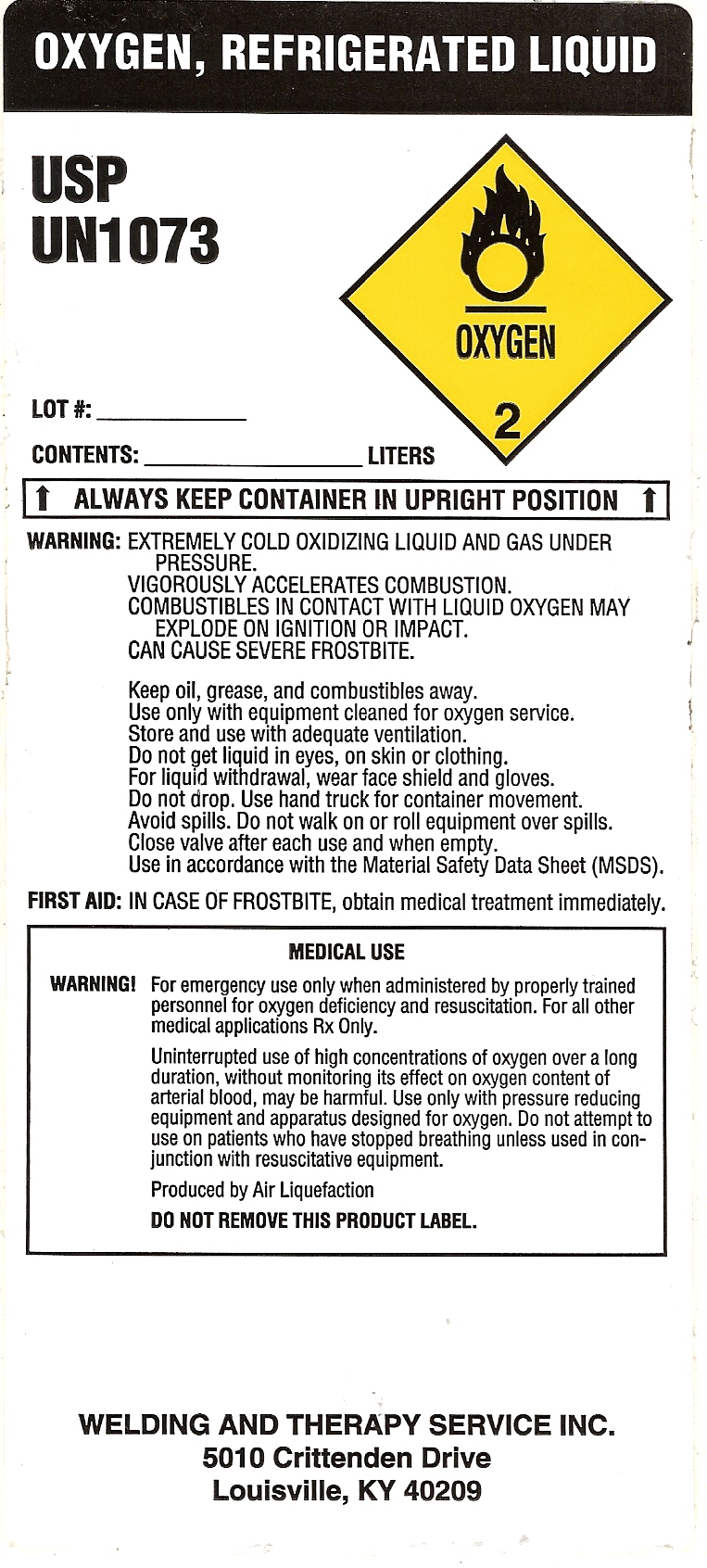 DRUG LABEL: Oxygen
NDC: 33344-006 | Form: LIQUID
Manufacturer: Welding & Therapy Service Inc.
Category: prescription | Type: HUMAN PRESCRIPTION DRUG LABEL
Date: 20110722

ACTIVE INGREDIENTS: Oxygen 99 L/100 L

OXYGEN LIQUID LABEL

PACKAGE LABEL

OXYGEN, REFRIGERATED LIQUID
USP
UN1073
LOT#:_______
CONTENTS:__________LITERS
OXYGEN 2
ALWAYS KEEP CONTAINER IN UPRIGHT POSITION
WARNING: EXTREMELY COLD OXIDIZING LIQUID AND GAS UNDER
PRESSURE.
VIGOROUSLY ACCELERATES COMBUSTION.
COMBUSTIBLES IN CONTACT WITH LIQUID OXYGEN MAY
EXPLODE ON IGNITION OR IMPACT.
CAN CAUSE SEVERE FROSTBITE.
Keep oil, grease, and combustibles away.
Use only with equipment cleaned for oxygen service.
Store and use with adequate ventilation.
Do not get liquid in eyes, on skin or clothing.
For liquid withdrawal, wear face shield and gloves.
Avoid spills. Do not walk on or roll equipment over spills.
Close valve after each use and when empty.
USe in accordance with the Material Safety Data Sheet (MSDS).
FIRST AID: IN CASE OF FROSTBITE, obtain medical treatment immediately.
MEDICAL USE
WARNING! For emergency use only when administered by properly trained
personnel for oxygen deficiency and resuscitation. For all other
medical applications Rx Only.
Uninterrupted use of high concentrations of oxygen over a long
duration, without monitoring its effect on oxygen content of
arterial blood, may be harmful. Use only with pressure reducing
equipment and apparatus designed for oxygen. Do not attempt to
use on patients who have stopped breathing unless used in
conjunction with resuscitative equipment.
Produced by Air Liquefaction
DO NOT REMOVE THIS PRODUCT LABEL.
WELDING AND THERAPY SERVICE INC.
5010 Crittenden Drive
Louisville, KY 40209